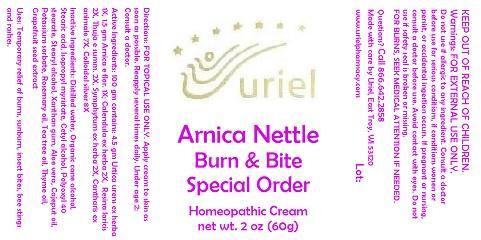 DRUG LABEL: Arnica Nettle Burn and Bite Special Order
NDC: 48951-1218 | Form: CREAM
Manufacturer: Uriel Pharmacy Inc.
Category: homeopathic | Type: HUMAN OTC DRUG LABEL
Date: 20140910

ACTIVE INGREDIENTS: URTICA URENS 1 [hp_X]/1 g; ARNICA MONTANA FLOWER 1 [hp_X]/1 g; CALENDULA OFFICINALIS FLOWERING TOP 2 [hp_X]/1 g; LARIX DECIDUA RESIN 2 [hp_X]/1 g; THUJA OCCIDENTALIS WHOLE 2 [hp_X]/1 g; COMFREY ROOT 2 [hp_X]/1 g; LYTTA VESICATORIA 7 [hp_X]/1 g; SILVER 8 [hp_X]/1 g
INACTIVE INGREDIENTS: WATER; ALCOHOL; STEARIC ACID; ISOPROPYL MYRISTATE; CETYL ALCOHOL; POLYOXYL 40 STEARATE; STEARYL ALCOHOL; XANTHAN GUM; ALOE VERA LEAF; CAJUPUT OIL; POTASSIUM SORBATE; ROSEMARY OIL; TEA TREE OIL; THYME OIL; CITRUS PARADISI SEED

Arnica Nettle Burn and Bite Special Order

INDICATIONS AND USAGE

Directions: FOR TOPICAL USE ONLY.

DOSAGE AND ADMINISTRATION

Apply cream to skin as soon as possible. Reapply several times daily. Under age 2: Consult a doctor.

ACTIVE INGREDIENT

Active Ingredients: 100 gm contains: 4.5 gm Urtica urens ex herba 1X, 1.5 gm Arnica e flor. 1X; Calendula ex herba 2X, Resina laricis 2X, Thuja e summ. 2X, Symphytum ex herba 2X, Cantharis ex animale 7X, Colloidal silver 8X

INACTIVE INGREDIENT

Inactive Ingredients: Distilled water, Organic cane alcohol, Stearic acid, Isopropyl myristate, Cetyl alcohol, Polyoxyl 40 stearate, Stearyl alcohol, Xanthan gum, Aloe vera, Cajeput oil, Potassium sorbate, Rosemary oil, Tea tree oil, Thyme oil, Grapefruit seed extract

PURPOSE

Uses: Temporary relief of burns, sunburn, insect bites, bee stings and rashes.

KEEP OUT OF REACH OF CHILDREN.

WARNINGS

Warnings: FOR EXTERNAL USE ONLY. Do not use if allergic to any ingredient. Consult a doctor before use for serious conditions, if conditions worsen or persist, or accidental ingestion occurs. If pregnant or nursing, consult a doctor before use. Avoid contact with eyes. Do not use if safety seal is broken or missing. FOR BURNS, SEEK MEDICAL ATTENTION IF NEEDED.

QUESTIONS

Questions? Call 866.642.2858 Made with care by Uriel, East Troy, WI 53120 www.urielpharmacy.com